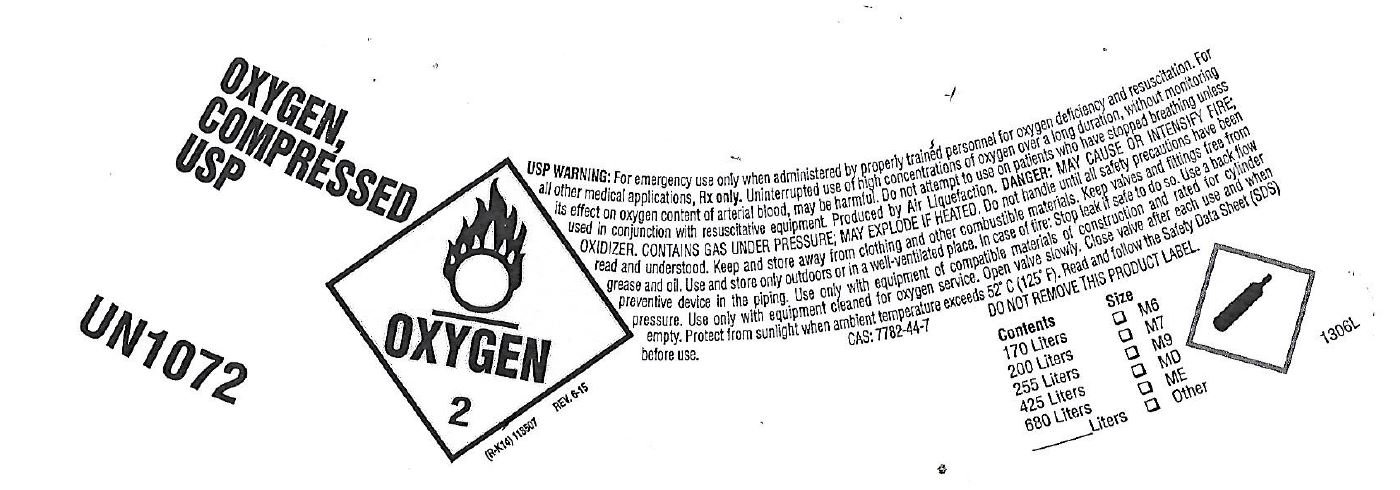 DRUG LABEL: Oxygen
NDC: 11928-002 | Form: GAS
Manufacturer: Mada Medical Products, Inc.
Category: prescription | Type: HUMAN PRESCRIPTION DRUG LABEL
Date: 20241120

ACTIVE INGREDIENTS: OXYGEN 1 L/1 L

11928-002 Oxygen

PACKAGE LABEL

OXYGEN,

COMPRESSED

USP

UN1072

OXYGEN

2

USP WARNING: For emergency use only when administered by properly trained personnel for oxygen deficiency and resuscitation. For all other medical applications, Rx only. Uninterrupted use of high concentrations of oxygen over a long duration, without monitoring its effects on oxygen content of arterial blood, may be hamful. Do not attempt to use on patients who have stopped breathing unless used in conjunction with resuscitative equipment. Produced by Air Liquefaction. DANGER: MAY CAUSE OR INTENSIFY FIRE; OXIDIZER. CONTAINS GAS UNDER PRESSURE, MAY EXPLODE IF HEATED. Do not handle until all safety precautions have been read and understood. Keep and store away from clothing and other combustible materials. Keep valves and fittings free from grease and oil. Use and store only outdoors or in a well-ventilated place. In case of fire: Stop leak if safe to do so. Use a back flow preventive device in the piping. Use only with equipment of compatible materials of construction and rated for cylinder pressure. Use only with equipment cleaned for oxygen service. Open valve slowly. Close valve after each use and when empty. Protect from sunlight whem ambient temperature exceeds 52 C (125 F). Read and follow the Safety Data Sheet (SDS) before use.

CAS: 7782-44-7

DO NOT REMOVE THIS PRODUCT LABEL

Contents Size

170 Liters M6

200 Liters M7

255 Liters M9

425 Liters MD

680 Liters ME

___ Liters Other